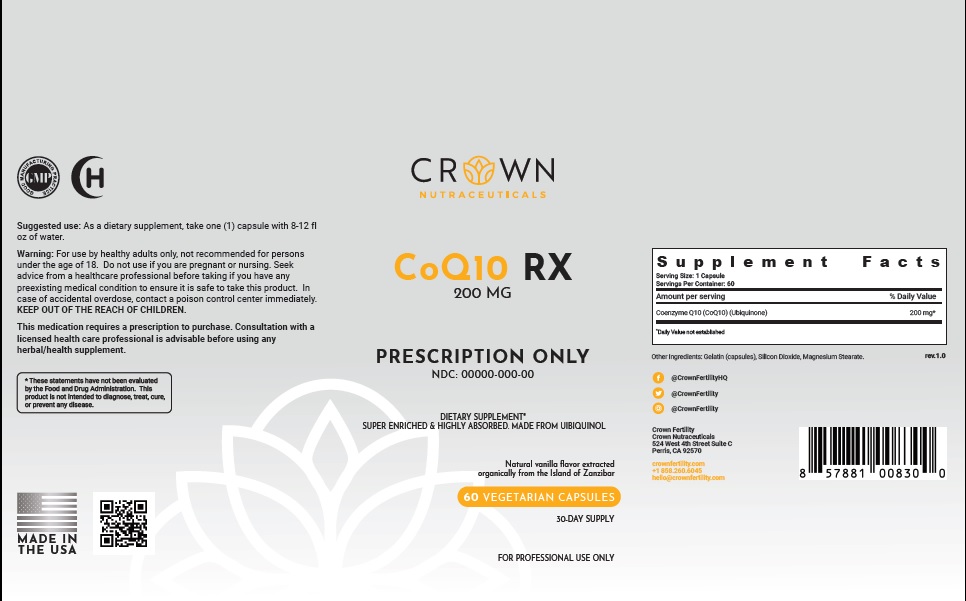 DRUG LABEL: CoQ10 200mg
NDC: 73489-007 | Form: CAPSULE
Manufacturer: CROWN GENERAL AGENCY INC
Category: other | Type: Dietary Supplement
Date: 20210318

ACTIVE INGREDIENTS: UBIDECARENONE 200 mg/1 1
INACTIVE INGREDIENTS: GELATIN, UNSPECIFIED; SILICON DIOXIDE; MAGNESIUM STEARATE

STATEMENT OF IDENTITY

Dietary Supplement

Suggested Use

As a dietary supplement, take one (1) capsule twice a day with 8-12 fl oz of water.

Coenzyme Q-10 deficiency.

Precaution

For use by healthy adults only, not recommended for persons
under the age of 18. Do not use if you are pregnant or nursing. Seek
advice from a healthcare professional before taking if you have any
preexisting medical condition to ensure it is safe to take this product. In
case of accidental overdose, contact a poison control center immediately.
KEEP OUT OF THE REACH OF CHILDREN.

If having surgery stop 14 days ahead of time.

This medication requires a prescription to purchase. Consultation with a
licensed health care professional is advisable before using any
herbal/health supplement.